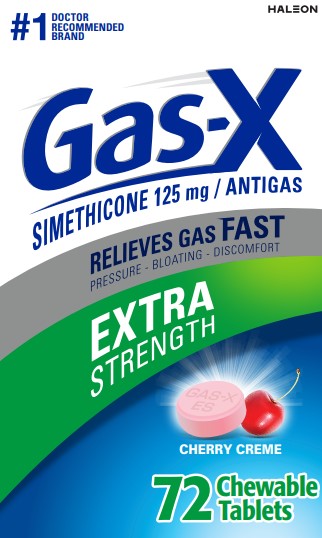 DRUG LABEL: Gas-X
NDC: 0067-0117 | Form: TABLET, CHEWABLE
Manufacturer: Haleon US Holdings LLC
Category: otc | Type: HUMAN OTC DRUG LABEL
Date: 20241213

ACTIVE INGREDIENTS: DIMETHICONE, UNSPECIFIED 125 mg/1 1
INACTIVE INGREDIENTS: TRIBASIC CALCIUM PHOSPHATE; SILICON DIOXIDE; D&C RED NO. 30; DEXTROSE, UNSPECIFIED FORM; MALTODEXTRIN; PROPYLENE GLYCOL; SOY PROTEIN

Drug Facts

Active ingredient (in each tablet)

Simethicone 125 mg

Purpose

Antigas

Use

for the relief of

• pressure, bloating, and fullness commonly referred to as gas

Directions

• adults and children 12 years and older: chew 1 or 2 tablets as needed after meals and at bedtime. Chew or crush tablets completely before swallowing.

• do not exceed 4 tablets in 24 hours except under the advice and supervision of a physician

Other information

• each chewable tablet contains: calcium 45 mg

• store at controlled room temperature 20-25°C (68-77°F)

• protect from moisture

Inactive ingredients

calcium phosphate tribasic, colloidal silicon dioxide, D&C Red 30 aluminum lake, dextrose, flavors, maltodextrin, propylene glycol, soy protein isolate

Questions or comments?

call 1-855-328-5204

Principal Display Panel

#1 DOCTOR RECOMMENDED BRAND

Gas-X

SIMETHICONE 125 mg /ANTIGAS

RELIEVES GAS FAST

Pressure • Bloating • Discomfort

EXTRA STRENGTH

CHERRY CREME

72 Chewable Tablets

Gas-X Extra Strength Cherry Creme chewable tablets have a pleasantly smooth, creamy cherry flavor. Chewable tablets are also available in a great tasting Peppermint Creme flavor.

TAMPER EVIDENT FEATURE:

Gas-X tablets are sealed in blister packets. Use only if the individual seal is unbroken.

Gas-XExtra Strength Tablets offer fast, effective relief of pressure and bloating that antacids can’t provide. They are specially formulated with simethicone, the antigas medicine doctors recommend most for pressure, bloating or discomfort referred to as gas.